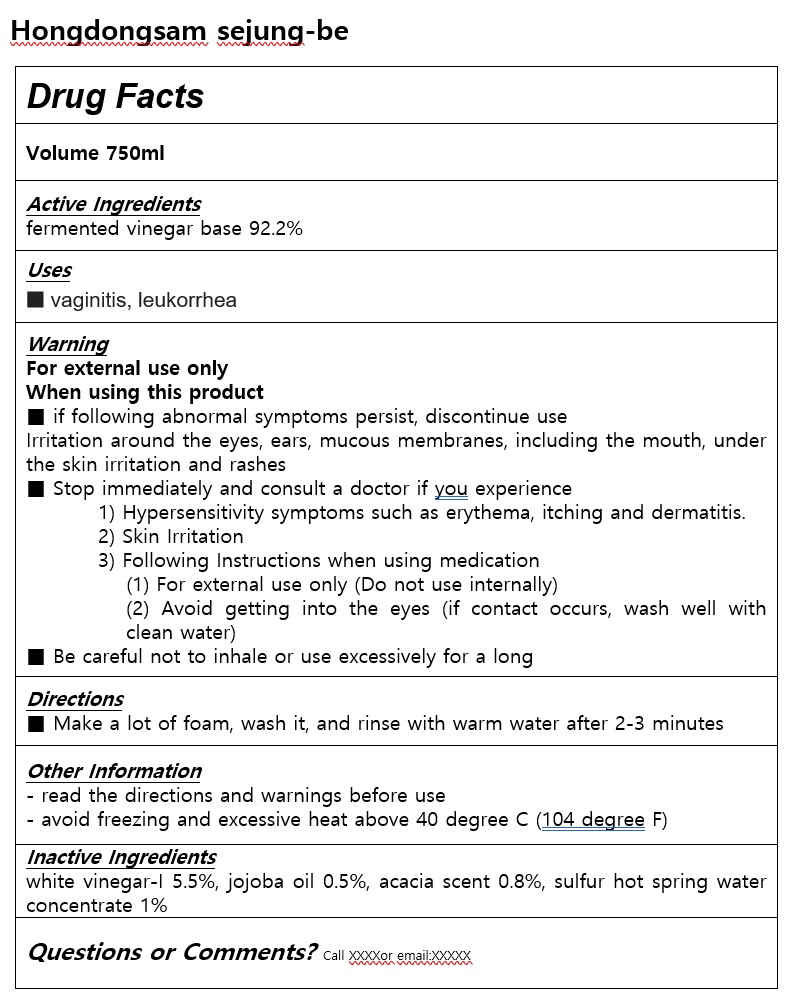 DRUG LABEL: Hongdongsam sejung-be
NDC: 84954-0003 | Form: SOAP
Manufacturer: Hyosungwon
Category: otc | Type: HUMAN OTC DRUG LABEL
Date: 20241118

ACTIVE INGREDIENTS: APPLE CIDER VINEGAR 92.2 g/100 mL
INACTIVE INGREDIENTS: JOJOBA OIL

Drug Facts

ACTIVE INGREDIENT

fermented vinegar base 92.2%

INACTIVE INGREDIENT

white vinegar-I 5.5%, jojoba oil 0.5%, acacia scent 0.8%, sulfur hot spring water concentrate 1%

PURPOSE

vaginitis, leukorrhea

keep out of reach of the children

INDICATIONS AND USAGE

Make a lot of foam, wash it, and rinse with warm water after 2-3 minutes

WARNINGS

For external use only

When using this product

■ if following abnormal symptoms persist, discontinue use

Irritation around the eyes, ears, mucous membranes, including the mouth, under the skin irritation and rashes

■ Stop immediately and consult a doctor if you experience

1) Hypersensitivity symptoms such as erythema, itching and dermatitis.

2) Skin Irritation

3) Following Instructions when using medication

(1) For external use only (Do not use internally)

(2) Avoid getting into the eyes (if contact occurs, wash well with clean water)

■ Be careful not to inhale or use excessively for a long

DOSAGE AND ADMINISTRATION

for topical use